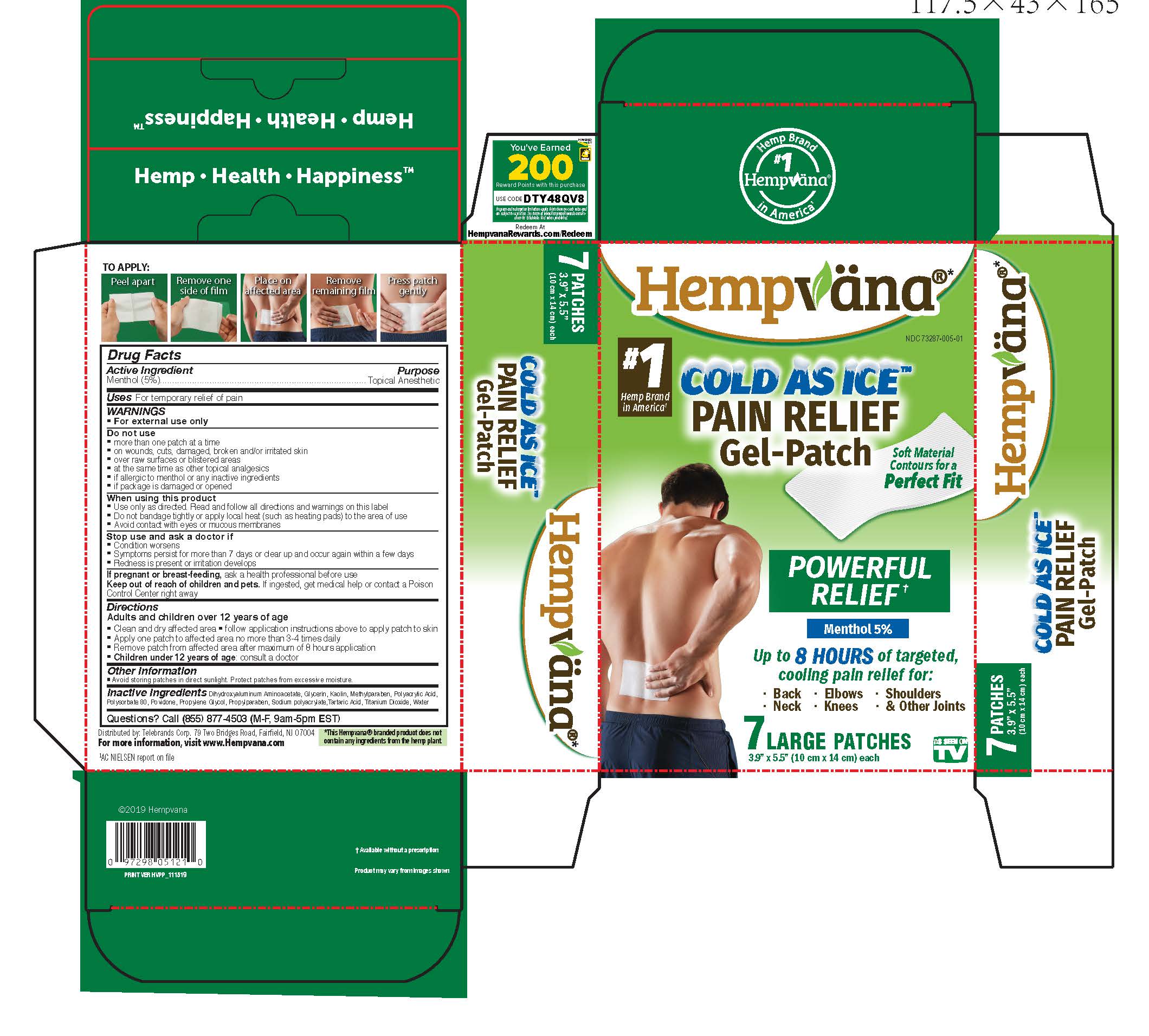 DRUG LABEL: Hempvana Cold As Ice
NDC: 73287-005 | Form: PATCH
Manufacturer: Telebrands Corp
Category: otc | Type: HUMAN OTC DRUG LABEL
Date: 20241120

ACTIVE INGREDIENTS: MENTHOL 5 g/100 g
INACTIVE INGREDIENTS: WATER; DIHYDROXYALUMINUM AMINOACETATE; GLYCERIN; KAOLIN; METHYLPARABEN; POLYACRYLIC ACID (250000 MW); POLYSORBATE 80; POVIDONE; PROPYLENE GLYCOL; PROPYLPARABEN; SODIUM POLYACRYLATE (2500000 MW); TARTARIC ACID; TITANIUM DIOXIDE

Hempvana Cold As Ice Pain Relief Gel-Patch

Active Ingredient:

Menthol 5%

Purpose

Menthol 5%................Topical Anesthetic

Uses

temporarily relief of pain

Warnings

For external use only

Do not use

- more than one patch at a time
- on wounds, cuts, damaged, broken and/or irritated skin
- over raw surfaces or blistered areas
- at the same time as other topical analgesics
- if allergic to menthol or any inactive ingredients
- if package is damaged or opened

When using this product

- Use only as directed. Read and follow all directions and warnings on this label
- Do not bandage tightly or apply local heat (such as heating pads) to the area of use
- Avoid contact with eyes or mucous membranes

Stop use and ask a doctor if

- Condition worsens
- Symptoms persist for more than 7 days or clear up and occur again within a few days
- Redness is present or irritation develops

PREGNANCY OR BREAST FEEDING

If pregnant or breast-feeding,ask a health professional before use

Keep out of reach of children and pets.If ingested, get medical help or contact a Poison Control Center right away

Directions

Adults and children over 12 years of age

- Clean and dry affected area
- follow application insructions above to apply patch to skin
- Apply one patch to affected area no more than 3-4 times daily
- Remove patch from affected area after maximum of 8 hour application
- Children uner 12 years of age: consult a doctor

STORAGE AND HANDLING

- Avoid storing patches in direct sunlight. Protect patches from excessive moisture

Inactive Ingredients

Dihydroxyaluminum Aminoacetate, Glycerin, Kaolin, Methylparaben, Polyacrylic Acid, Polysorbate 80, Povidone, Propylene Glycol, Propylparaben, Sodium polyacrylate,Tartaric Acid, Titanium Dioxide, Water

Questions?

Call (855) 877-4503 (M-F, 9am-5pm EST)